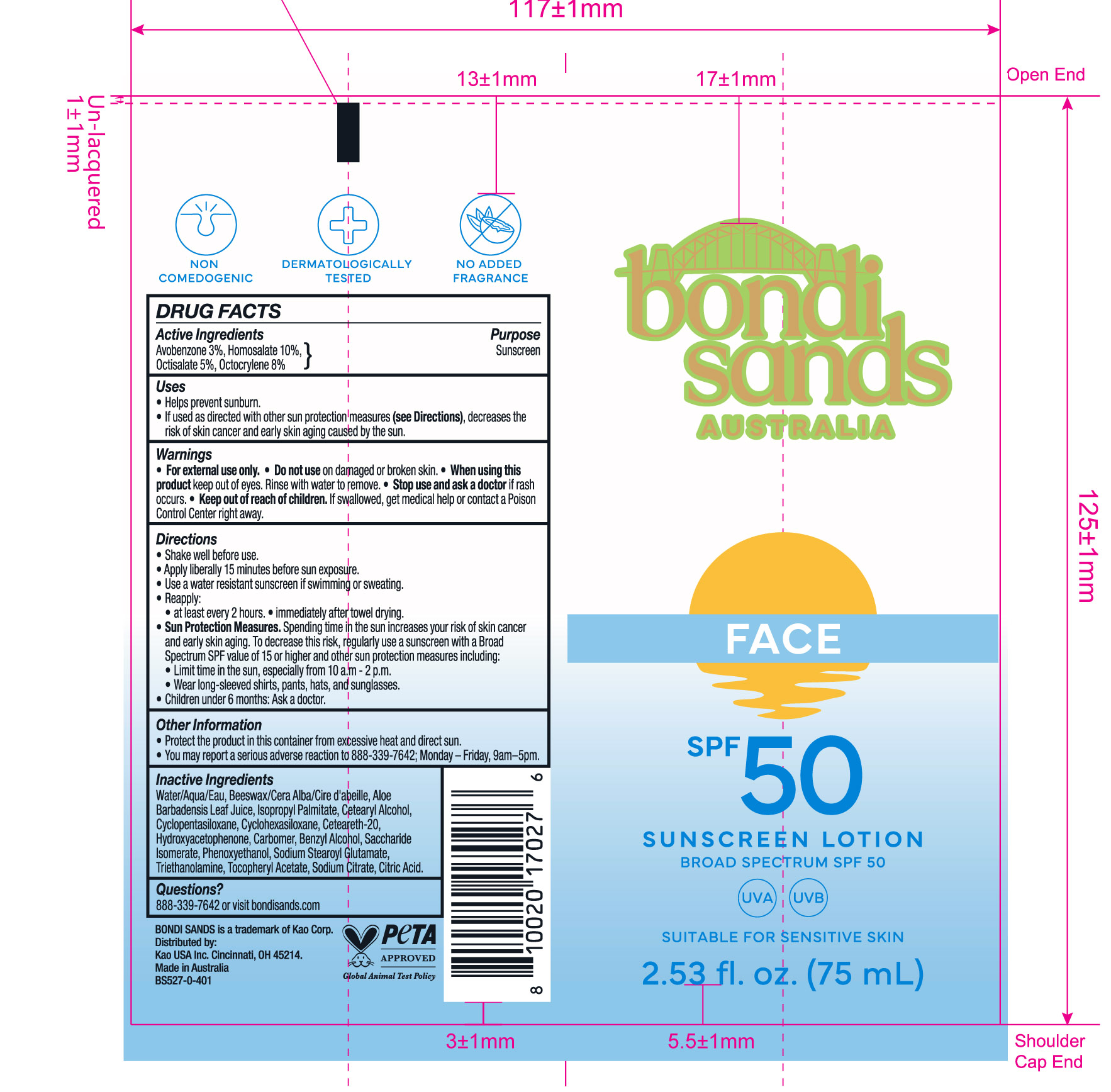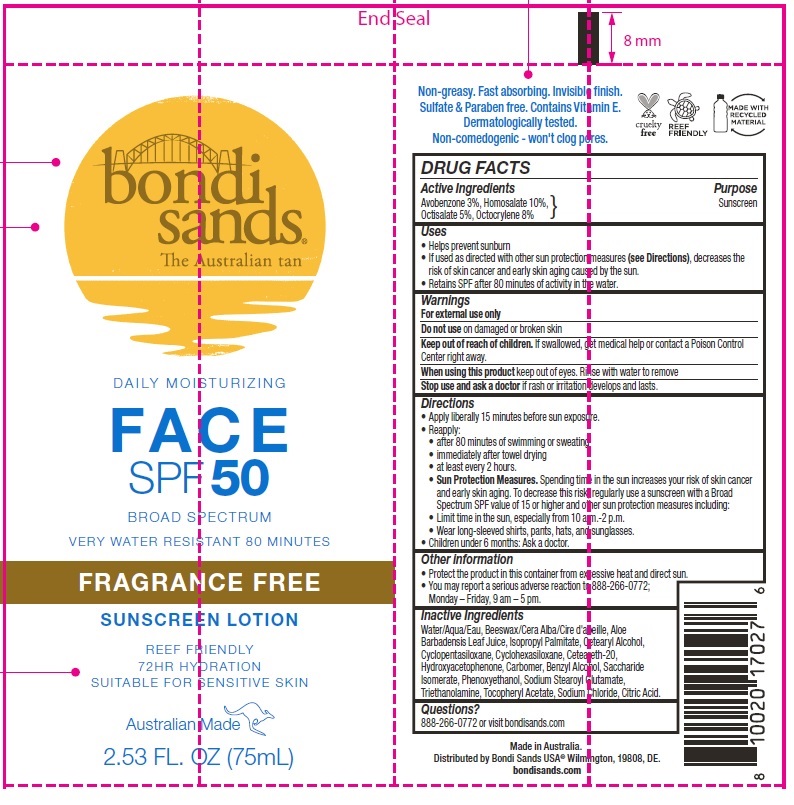 DRUG LABEL: Bondi Sands Fragrance Free Face SPF 50 Sunscreen
NDC: 70157-014 | Form: LOTION
Manufacturer: Baxter Laboratories Pty. Ltd.
Category: otc | Type: HUMAN OTC DRUG LABEL
Date: 20251029

ACTIVE INGREDIENTS: AVOBENZONE 30 mg/1 mL; OCTOCRYLENE 80 mg/1 mL; HOMOSALATE 100 mg/1 mL; OCTISALATE 50 mg/1 mL
INACTIVE INGREDIENTS: SODIUM STEAROYL GLUTAMATE; SACCHARIDE ISOMERATE; BENZYL ALCOHOL; CARBOMER HOMOPOLYMER, UNSPECIFIED TYPE; WATER; ALOE VERA LEAF; .ALPHA.-TOCOPHEROL ACETATE; ISOPROPYL PALMITATE; CETOSTEARYL ALCOHOL; CYCLOMETHICONE 5; CYCLOMETHICONE 6; POLYOXYL 20 CETOSTEARYL ETHER; HYDROXYACETOPHENONE; YELLOW WAX; CITRIC ACID MONOHYDRATE; TROLAMINE; SODIUM CHLORIDE; PHENOXYETHANOL

Bondi Sands Fragrance Free Face SPF 50 Sunscreen Lotion

Active Ingredients

Avobenzone 3%, Homosalate 10%, Octisalate 5%, Octocrylene 8%

Purpose

Sunscreen

Uses

- Helps prevent sunburn
- If used as directed with other sun protections measures (see Directions), decreases the risk of cancer and early skin aging caused by the sun.
- Retains SPF after 80 minutes of activity in the water.

Warnings

For external use only

Keep out of reach of children.

If swallowed, get medical help or contact a Poison Control Center right away.

When using this product

keep out of eyes. Rinse with water to remove.

Directions

- Apply liberally 15 minutes before sun exposure.
- Reapply:
- after 80 minutes of swimming or sweating
- immediately after towel drying
- at least every 2 hours
- Sun Protection Measures. Spending time in the sun increases your risk of skin cancer and early skin aging. To decrease this risk, regularly use a sunscreen with a Broad Spectrum SPF value of 15 or higher and other sun protection measures including:
- Limit time in the sun, especially from 10 a.m.- 2 p.m.
- Wear long-sleeved shirts, pants, hats, and sunglasses.
- Children under 6 months: Ask a doctor.

Other information

- Protect the product in this container from excessive heat and direct sun.
- You may report a serious adverse reaction to 888-266-0772; Monday – Friday, 9 am – 5 pm.

Inactive Ingredients

Water/Aqua/Eau, Beeswax/Cera Alba/Cire d'abeille, Aloe Barbadensis Leaf Juice, Isopropyl Palmitate, Cetearyl Alcohol, Cyclopentasiloxane, Cyclohexasiloxane, Ceteareth-20, Hydroxyacetophenone, Carbomer, Benzyl Alcohol, Saccharide Isomerate, Phenoxyethanol, Sodium Stearoyl Glutamate, Triethanolamine, Tocopheryl Acetate, Sodium Chloride, Citric Acid.

Questions?

888-266-0772 or visit bondisands.com

Product Packaging

bondi sands

FACE

SPF 50

BROAD SPECTRUM

SUNSCREEN LOTION

SUITABLE FOR SENSITIVE SKIN

2.53 FL. OZ. (75mL)